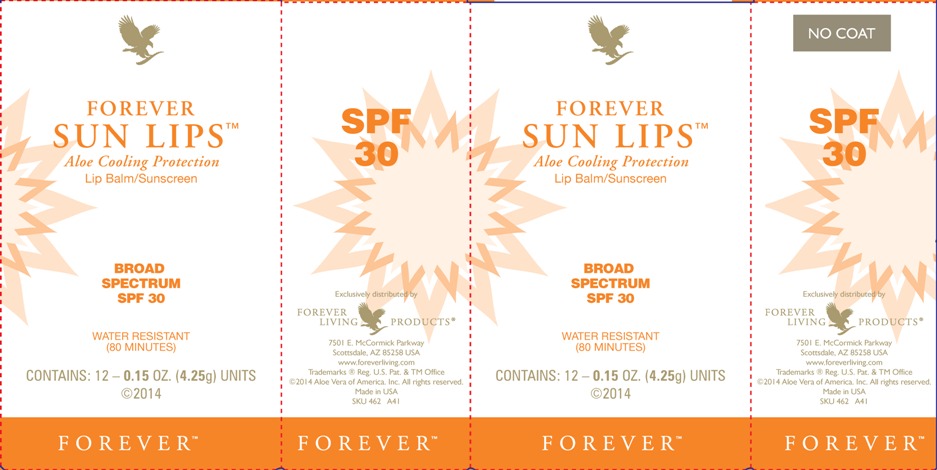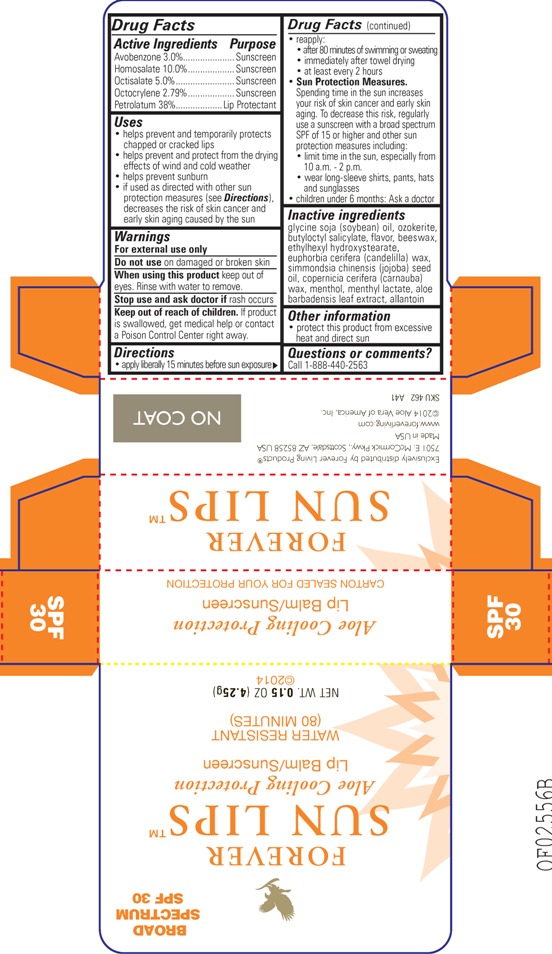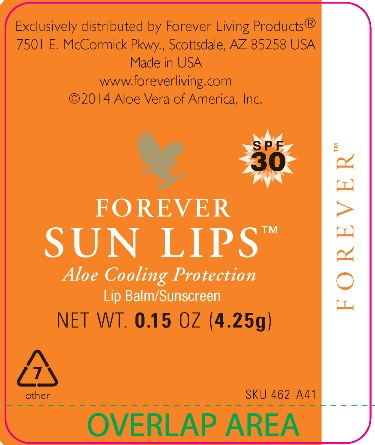 DRUG LABEL: Forever Sun Lips
NDC: 11697-462 | Form: LIPSTICK
Manufacturer: Aloe Vera of America, Inc.
Category: otc | Type: HUMAN OTC DRUG LABEL
Date: 20140325

ACTIVE INGREDIENTS: AVOBENZONE 0.1275 g/4.25 g; HOMOSALATE 0.4250 g/4.25 g; OCTISALATE 0.2125 g/4.25 g; OCTOCRYLENE 0.1186 g/4.25 g; PETROLATUM 1.6150 g/4.25 g
INACTIVE INGREDIENTS: SOYBEAN OIL .4473 g/4.25 g; CERESIN .3868 g/4.25 g; BUTYLOCTYL SALICYLATE .2295 g/4.25 g; YELLOW WAX .1275 g/4.25 g; ETHYLHEXYL HYDROXYSTEARATE .1148 g/4.25 g; CANDELILLA WAX .1063 g/4.25 g; JOJOBA OIL .0850 g/4.25 g; CARNAUBA WAX .0425 g/4.25 g; MENTHOL .0223 g/4.25 g; MENTHYL LACTATE, (-)- .0223 g/4.25 g; ALOE VERA LEAF .0138 g/4.25 g; ALLANTOIN .0004 g/4.25 g

Forever Sun Lips

Active Ingredients | Purpose
Avobenzone 3.0%.................. | Sunscreen
Homosalate 10.0%................ | Sunscreen
Octisalate 5.0%..................... | Sunscreen
Octocrylene 2.79%................ | Sunscreen
Petrolatum 38%.................... | Lip Protectant

Uses

- helps prevent and temporarily protects chapped or cracked lips
- helps prevent and protect from the drying effects of wind and cold weather
- helps prevent sunburn
- if used as directed with other sun protection measures (see Directions), decreases the risk of skin cancer and early skin aging caused by the sun

Warnings

For external use only

Do not use on damaged and broken skin

When using this product keep out of eyes. Rinse with water to remove.

Stop use and ask doctor if rash occurs

Keep out of reach of children. If product is swallowed, get medical help or contact a Poison Control Center right away.

Directions

- apply liberally 15 minutes before sun exposure
- reapply:
- after 80 minutes of swimming or sweating
- immediately after towel drying
- at least every 2 hours
- Sun Protection Measures.

Spending time in the sun increases your risk of skin cancer and early skin aging. To decrease this risk, regularly use a sunscreen with a broad spectrum SPF of 15 or higher and other sun protection measures including:

- limit time in the sun, especially from 10 a.m. - 2 p.m.
- wear long-sleeve shirts, pants, hats and sunglasses
- children under 6 months: Ask a doctor

Inactive ingredients

glycine soja (soybean) oil, ozokerite, butyloctyl salicylate, flavor, beeswax, ethylhexyl hydroxystearate, euphorbia cerifera (candelilla) wax, simmondsia chinensis (jojoba) seed oil, copernicia cerifera (carnauba) wax, menthol, menthyl lactate, aloe barbadensis leaf extract, allantoin

Other information

- protect this product from excessive heat and direct sun

Questions or comments?

Call 1-888-440-2563